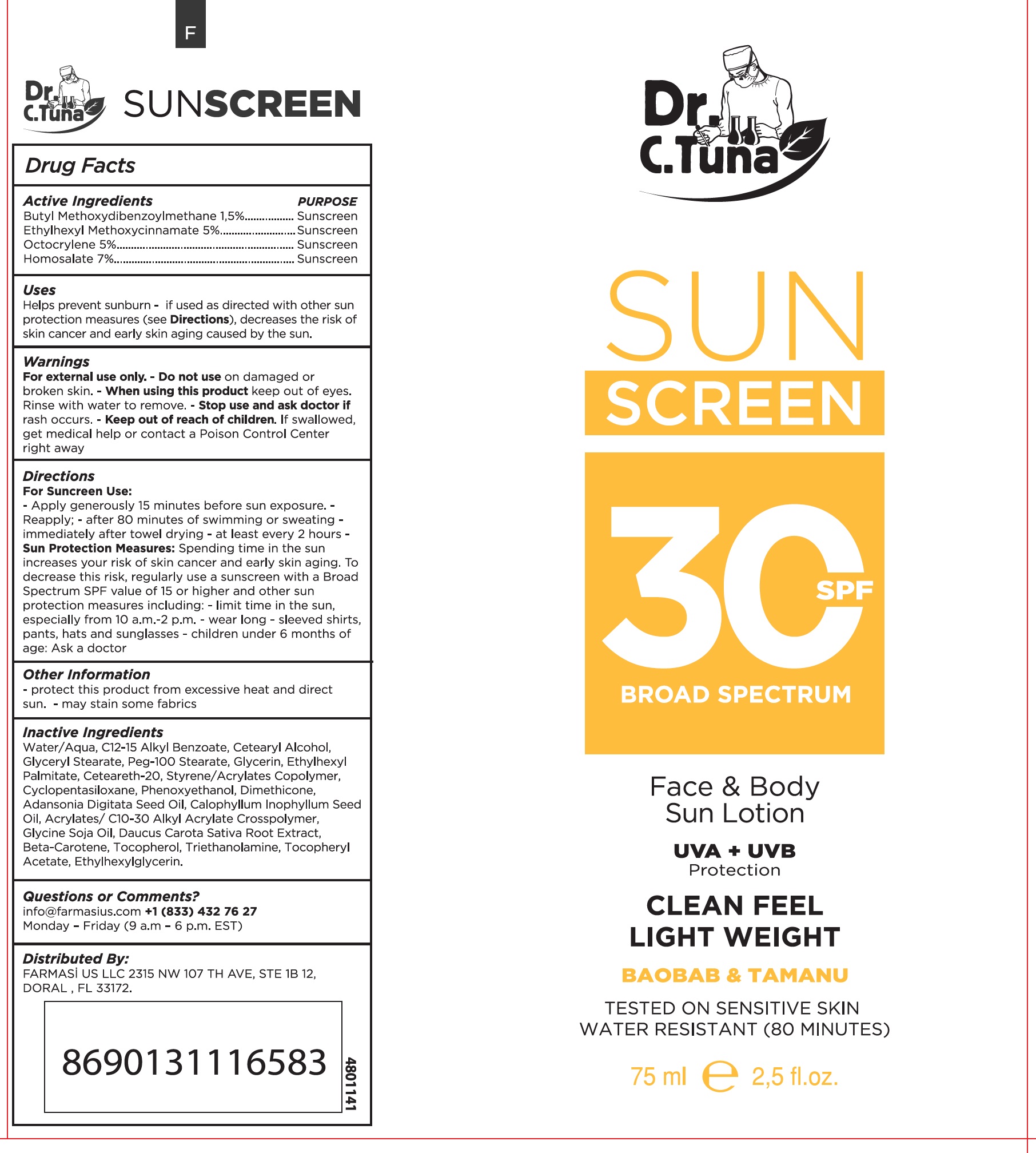 DRUG LABEL: DR. C Tuna Sunscreen 30 SPF Broad Spectrum Face and body
NDC: 78317-000 | Form: CREAM
Manufacturer: TAN-ALIZE KOZMETIK VE TEMIZLIK URUNLERI SANAYI VE TICARET ANONIM SIRKETI
Category: otc | Type: HUMAN OTC DRUG LABEL
Date: 20231105

ACTIVE INGREDIENTS: AVOBENZONE 15 mg/1 mL; OCTINOXATE 50 mg/1 mL; OCTOCRYLENE 50 mg/1 mL; HOMOSALATE 70 mg/1 mL
INACTIVE INGREDIENTS: WATER; ALKYL (C12-15) BENZOATE; CETOSTEARYL ALCOHOL; GLYCERYL MONOSTEARATE; PEG-100 STEARATE; GLYCERIN; ETHYLHEXYL PALMITATE; POLYOXYL 20 CETOSTEARYL ETHER; STYRENE; CYCLOMETHICONE 5; PHENOXYETHANOL; DIMETHICONE; ADANSONIA DIGITATA SEED OIL; TAMANU OIL; ACRYLIC ACID; SOYBEAN OIL; CARROT; BETA CAROTENE; TOCOPHEROL; TROLAMINE; .ALPHA.-TOCOPHEROL ACETATE; ETHYLHEXYLGLYCERIN

DR. C Tuna Sunscreen 30 SPF Broad Spectrum Face and body, 75mL

Active Ingredients

Butyl Methoxydibenzoylmethane 1.5% ethylhexyl Methoxycinnamate 5%, Octocrylene 5%, Homosalate 7%

purpose

Sunscreen

Uses

Helps prevent sunburn - if used as directed with other sun protection measures (see Directions), decreases the risk of skin cancer and early skin aging caused by the sun.

Warnings

For external use only.

-Do not use

on damaged or broken skin.

-When using this product

keep out of eyes. Rinse with water to remove.

-Stop use and ask doctor if

rash occurs.

-Keep out of reach of children.

If swallowed, get medical help or contact a Poison Control Centre right away

Directions

For suncreen use:

-Applygenerously 15 minutes before sun exposure.

- Reapply; - after 80 minutes of swimming or sweating

- immediately after towel drying - at least every 2 hours

; Spending time in the sun increase your risk of skin cancer and early skin aging. To decrease this risk, regular use a sunscreen with a Broad Spectrum SPF value of 15 or higher and other sun protection measures including; - limit in the sun, especially from 10 a.m -2 p.m. - wear long - sleeved shirts, pants, hats and sun glasses - children under 6 months of age: Ask a doctor Sun Protection Measures

Other information

- protect this product from excessive heat and direct sun.

- may stain some fabrics

Inactive Ingredients

water/Aqua, C12-15 Alkyl Benzoate, Cetearyl Alcohol, Glyceryl Stearate, Peg-100 Stearate, Glycerin, Ethylhexyl Palmitate,Ceteareth-20, Styrene/Acrylates Copolymer, Cyclopentasiloxane, Phenoxyethonol, Dimethicone, Adansonia digitata Seed Oil, Calophyllum inophyllum Seed Oil, Acrylates/ C10-30 Alkyl Acrylate Crosspolymer, Glycine Soja Oil, Daucus Carota Sativa Root Extract, Beta-Carotene, Tocopherol, Triethanolamine, Tocopheryl Acetate, ethlhexylglycerin.

Questions or comments?

info@farmasius.com +1 (833) 432 76 27

Monday - Friday (9 a.m - 6 p.m. EST)